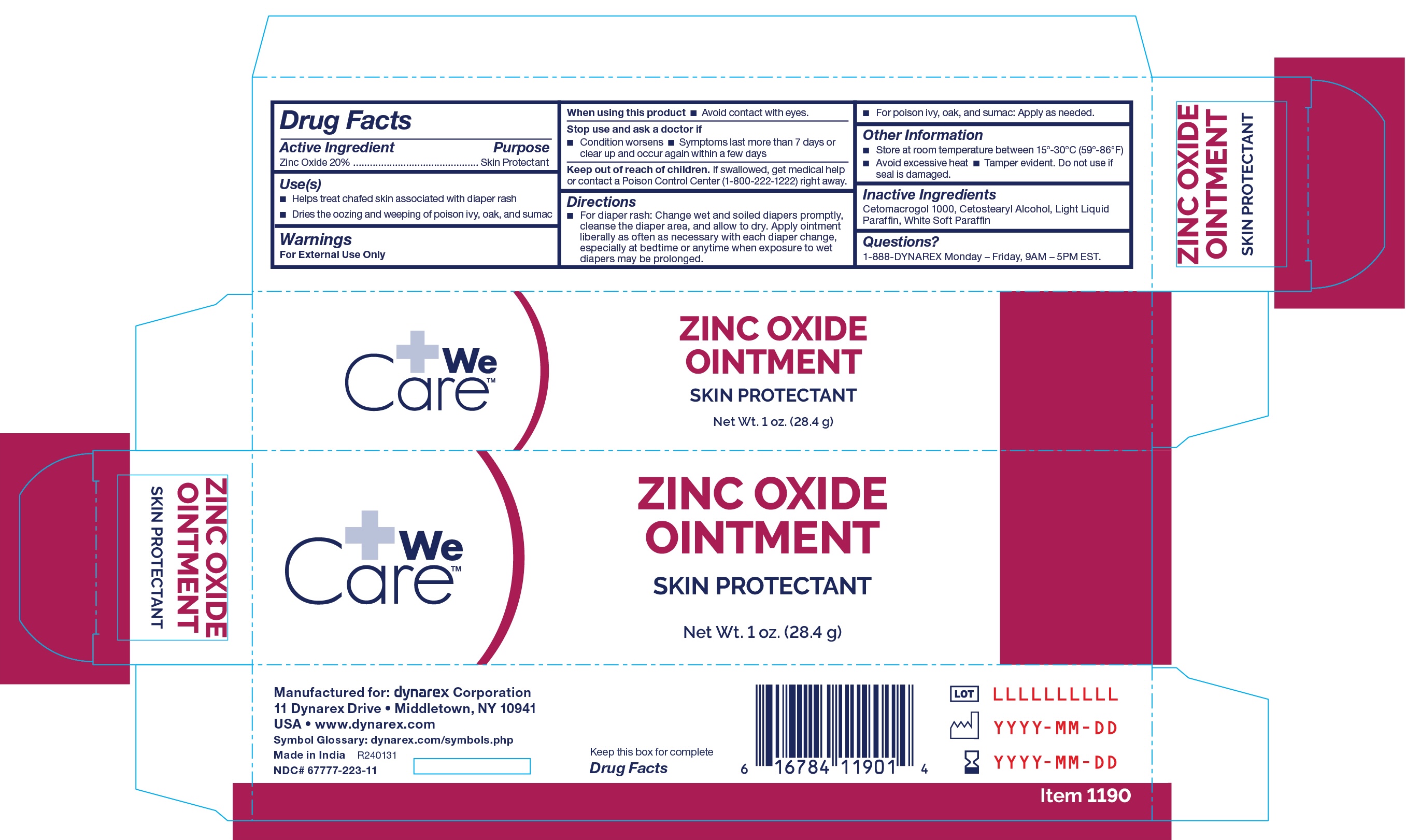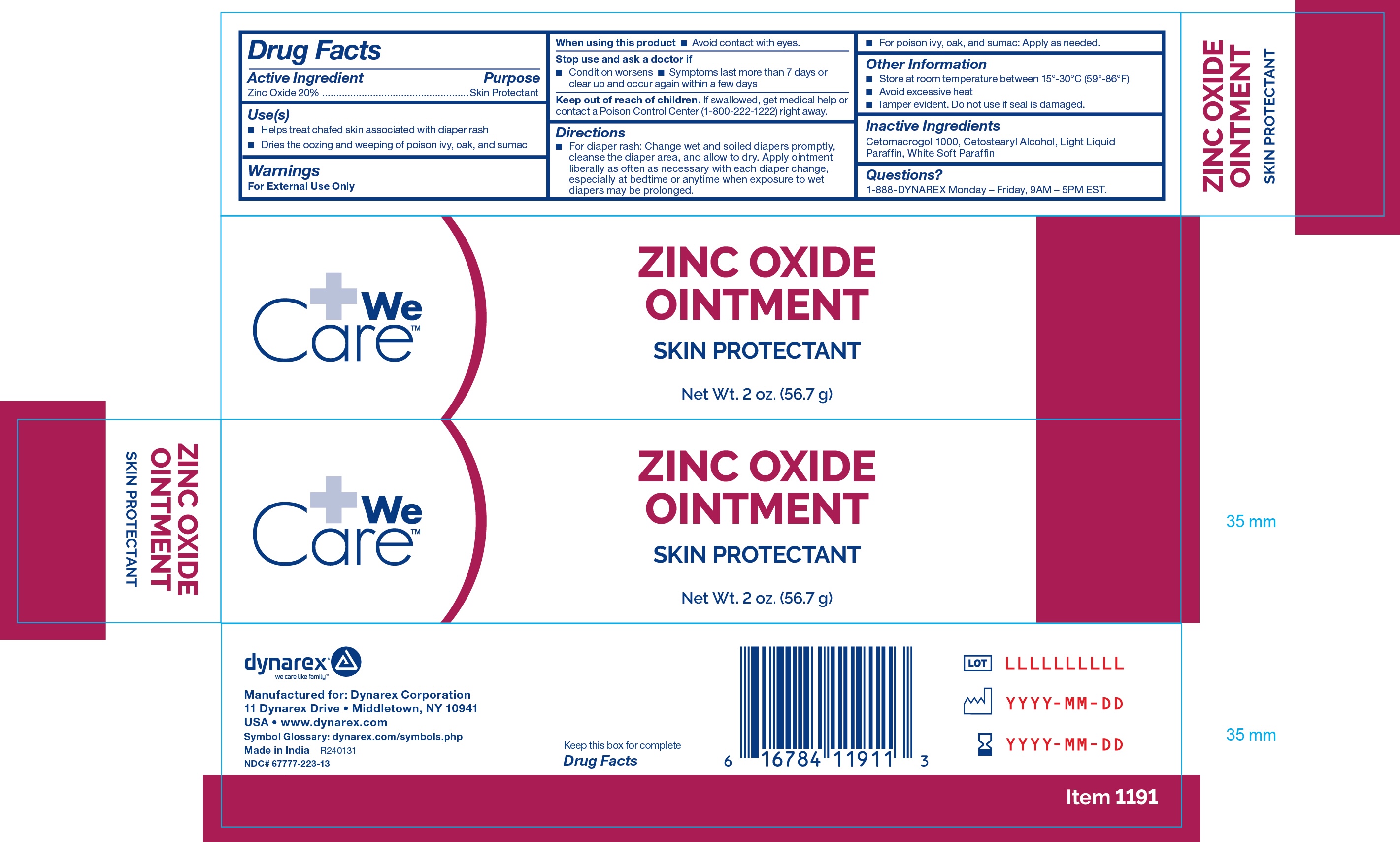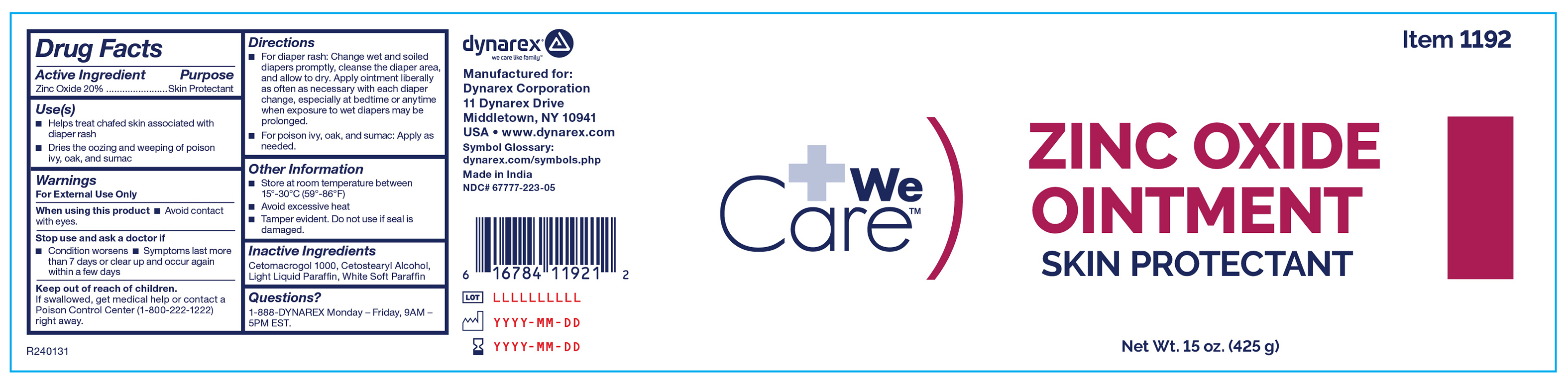 DRUG LABEL: Zinc Oxide
NDC: 67777-223 | Form: OINTMENT
Manufacturer: Dynarex Corporation
Category: otc | Type: HUMAN OTC DRUG LABEL
Date: 20240220

ACTIVE INGREDIENTS: ZINC OXIDE 200 mg/1 g
INACTIVE INGREDIENTS: WHITE PETROLATUM; LIGHT MINERAL OIL; CETETH-20; CETOSTEARYL ALCOHOL

1190, 1191, 1192 Zinc Oxide Ointment 20%

Active Ingredient

Zinc Oxide 20%

Purpose

Skin Protectant

Use(s)

• Helps treat chafed skin associated with diaper rash

• Dries the oozing and weeping of poison ivy, oak, and sumac

Warnings

For External Use Only

When using this product

• Avoid contact with eyes.

Stop use and ask a doctor if

• Condition worsens • Symptoms last more than 7 days or clear up and occur again within a few days

Keep out of reach of children

If swallowed, get medical help or contact a Poison Control Center (1-800-222-1222) right away.

Directions

• For diaper rash: Change wet and soiled diapers promptly, cleanse the diaper area, and allow to dry. Apply ointment liberally as often as necessary with each diaper change, especially at bedtime or anytime when exposure to wet diapers may be prolonged.

• For poison ivy, oak, and sumac: Apply as needed.

Other Information

• Store at room temperature between 15º-30ºC (59º-86ºF)

• Avoid excessive heat

• Tamper evident. Do not use if seal is damaged.

Inactive Ingredients

Cetomacrogol 1000. Cetostearyl Alcohol Light Liquid Paraffin, White Soft Paraffin

Questions?

1-888-Dynarex Monday - Friday, 9AM - 5PM EST.

Label

Label 1192

Label

Label 1190

Label

Label 1191